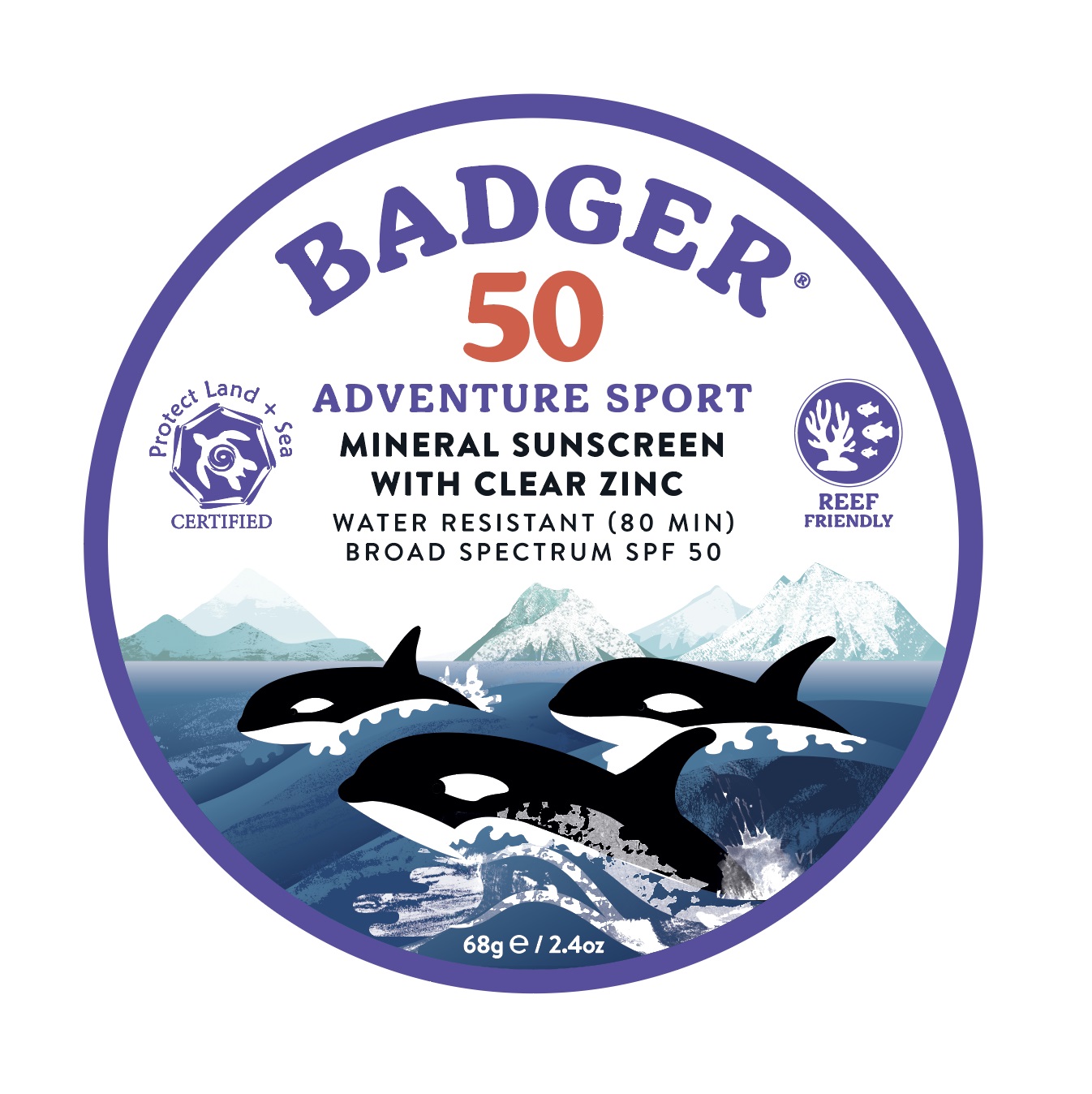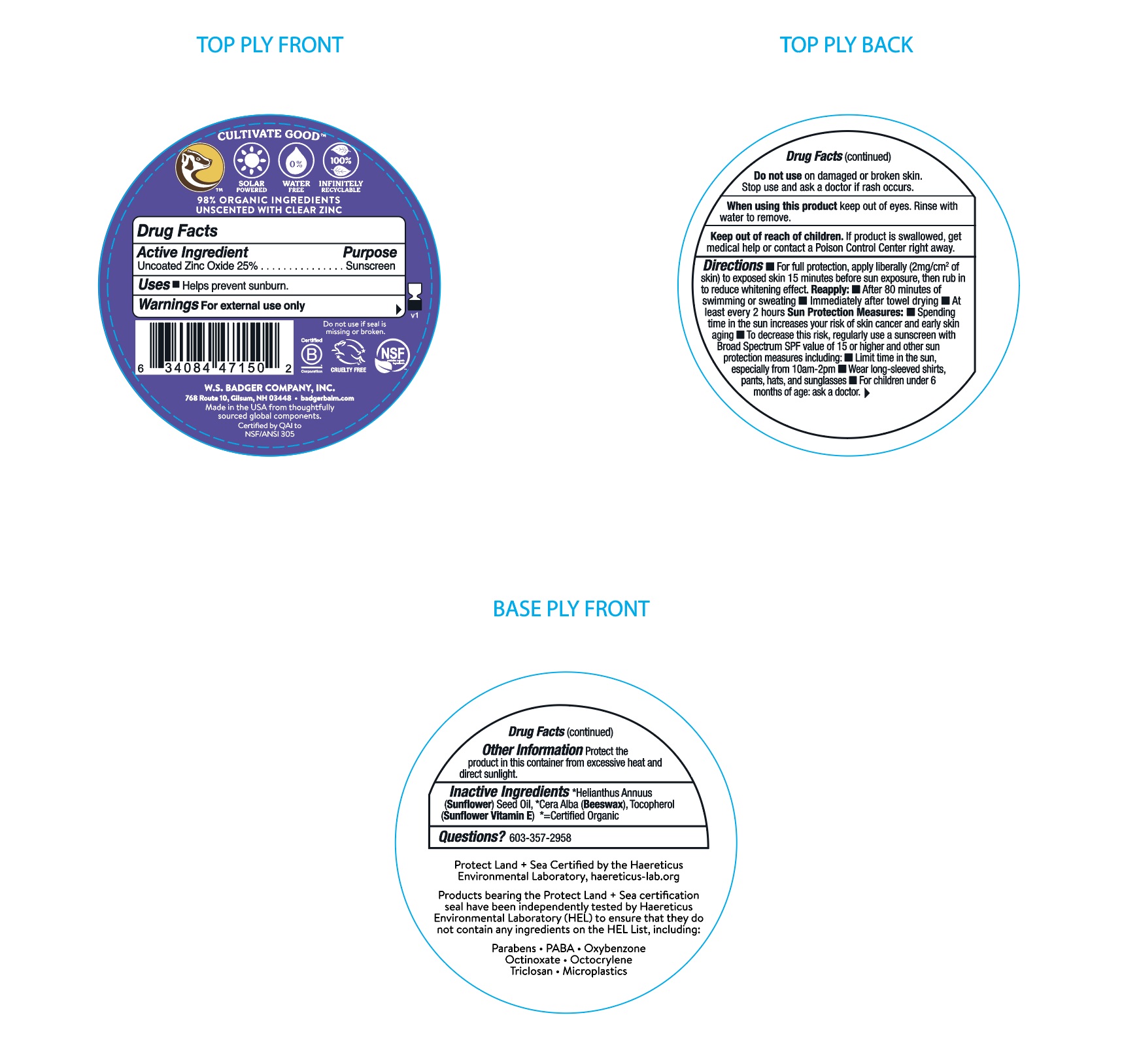 DRUG LABEL: Badger Adventure Sport Clear Mineral Sunscreen SPF 50
NDC: 62206-5023 | Form: CREAM
Manufacturer: W.S. Badger Company, Inc.
Category: otc | Type: HUMAN OTC DRUG LABEL
Date: 20241231

ACTIVE INGREDIENTS: ZINC OXIDE 25 g/100 g
INACTIVE INGREDIENTS: SUNFLOWER OIL; YELLOW WAX; TOCOPHEROL

Badger® SPF 50 Adventure Sport MIneral Sunscreen Tin

Drug Facts

Active Ingredient

Non-Nano Uncoated Zinc Oxide 25%

Purpose

Sunscreen

Uses

- Helps prevent sunburn
- If used as directed with other sun protection measures (see Directions), decreases the risk of skin cancer and early skin aging caused by the sun.

Warnings

For external use only

Do not use on damaged or broken skin. Stop use and ask a doctor if rash occurs.

When using this product keep out of eyes. Rinse with water to remove.

Keep out of reach of children. If product is swallowed, get medical help or contact a Poison Control Center right away.

Directions

- For full protection, apply liberally (2mg/cm^2 of skin) to all exposed skin 15 minutes before sun exposure, then rub in to reduce whitening effect.

Reapply:

- After 80 minutes of swimming or sweating
- Immediately after towel drying
- At least every 2 hours

Sun Protection Measures:

- Spending time in the sun increases your risk of skin cancer and early skin aging
- To decrease this risk, regularly use a sunscreen with a broad spectrum SPF value of 15 or higher and other sun protection measures including:
  - Limit time in the sun, especially from 10am-2pm
  - Wear long-sleeved shirts, pants, hats, and sunglasses
- For children under 6 months of age: ask a doctor.

Inactive Ingredients

*Helianthus Annuus (Sunflower) Seed Oil, *Cera Alba (Beeswax), Tocopherol (Sunflower Vitamin E), *= Organic

Other Information

Protect the product in this container from excessive heat and direct sunlight.

PRINCIPAL DISPLAY PANEL - 87 mL Tube Label

BADGER ® Adventure Sport

Mineral Sunscreen Cream with Clear Zinc

Unscented & Hypoallergenic

Broad Spectrum

SPF 50

WATER RESISTANT 80 min

Powered by Solar

Gluten Free

NON GMO

Cruelty Free

NSF

Certified B Corporation

REEF FRIENDLY

Protect Land + Sea Certified

98% Organic Ingredients

Natural Minerals

68gml/2.4 oz